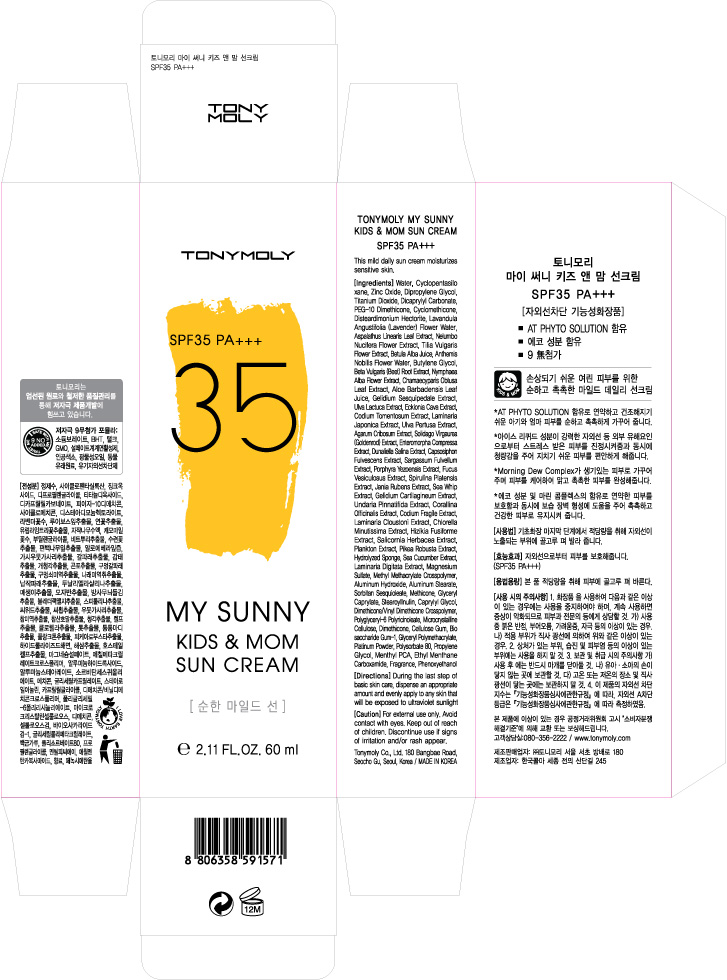 DRUG LABEL: TONYMOLY My Sunny All In One Sun SPF45
NDC: 59078-125 | Form: CREAM
Manufacturer: Tonymoly Co., Ltd.
Category: otc | Type: HUMAN OTC DRUG LABEL
Date: 20160204

ACTIVE INGREDIENTS: TITANIUM DIOXIDE 17977.5 mg/100 mL; GLYCERIN 8145.73 mg/100 mL; OCTOCRYLENE 2100 mg/100 mL
INACTIVE INGREDIENTS: PRUNUS MUME FRUIT; GELIDIUM CARTILAGINEUM; SQUALANE; PORTULACA OLERACEA WHOLE; ENZACAMENE; CYCLOMETHICONE 6; GLYCERYL MONOSTEARATE; PEG-100 STEARATE; ORANGE; OCTISALATE; CETOSTEARYL ALCOHOL; CHAMAEMELUM NOBILE FLOWER; ULVA COMPRESSA; COCO GLUCOSIDE; VANILLA; BENZYL ALCOHOL; GLYCERYL CAPRYLATE; MACROCYSTIS PYRIFERA; ECKLONIA CAVA; LAMINARIA JAPONICA; NYMPHAEA ALBA FLOWER; VISCUM ALBUM FRUIT; POTASSIUM SORBATE; SORBITAN SESQUIOLEATE; TROMETHAMINE; DIMETHICONE; CHAMAECYPARIS OBTUSA LEAF; SANSEVIERIA TRIFASCIATA LEAF; ETHYLHEXYLGLYCERIN; DEHYDROACETIC ACID; SODIUM BENZOATE; ACETYL TETRAPEPTIDE-15; WATER; BUTYLENE GLYCOL; NEOPENTYL GLYCOL DIHEPTANOATE; ALOE VERA LEAF; POTASSIUM CETYL PHOSPHATE; PEG-2 STEARATE; CAPRYLYL GLYCOL; ETHYLHEXYL PALMITATE; GLYCOL STEARATE; PHENOXYETHANOL; LAVANDULA ANGUSTIFOLIA FLOWER; DIPROPYLENE GLYCOL; SODIUM PALMITOYL PROLINE; CODIUM TOMENTOSUM; SORBIC ACID; VISCUM ALBUM WHOLE; AVOBENZONE

Active Ingredients

Ethylhexyl Methoxycinnamate 7.50%, Glycerin 6.47%, Octocrylene 2.00%, Titanium Dioxide 4.25%

Purpose

Sunscreen

Use

The all-in-one sun helps restore natural tone by providing moisture to the skin.

Caution

For external use only. Avoid contact with eyes. Keep out of reach of children. Discontinue use if signs of irritation and/or rash appear.

Keep out of reach of children

Directions

During the last step of basic skin care, dispense an appropriate amount and evenly apply to any skin that will be exposed to ultraviolet sunlight.

Inactive Ingredients

Water, Ethylhexyl Palmitate, Cyclopentasiloxane, 4-Methylbenzylidene Camphor, Butyl Methoxydibenzoylmethane, Cyclohexasiloxane, Butylene Glycol, Neopentyl Glycol Diheptanoate, Ethylhexyl Salicylate, Polymethyl Methacrylate, Cetearyl Alcohol, Glyceryl Stearate, PEG-100 Stearate, Triceteareth-4 Phosphate, Glycol Stearate, Silica, Sorbitan Sesquioleate, Potassium Cetyl Phosphate, PEG-2 Stearate, Tromethamine, Phenoxyethanol, Glyceryl Caprylate, Fragrance(Parfum), Acrylates/C10-30 Alkyl Acrylate Crosspolymer, Acrylates Copolymer, Caprylyl Glycol, Dimethicone, Iron Oxides (CI 77492), Disodium EDTA, Iron Oxides (CI 77491), Aloe Barbadensis Leaf Juice, Lavandula Angustifolia (Lavender) Water, Anthemis Nobilis Flower Water, Polydecene, Dipropylene Glycol, Prunus Mume Fruit Extract, Citrus Aurantium Dulcis (Orange) Fruit Extract, Sodium Palmitoyl Proline, Codium Tomentosum Extract, Enteromorpha Compressa Extract, Macrocystis Pyrifera (Kelp) Extract, Ecklonia Cava Extract, Gelidium Cartilagineum Extract, Laminaria Japonica Extract, Nymphaea Alba Flower Extract, Squalane, Chamaecyparis Obtusa Leaf Extract, Viscum Album (Mistletoe) Fruit Extract, Coco-Glucoside, Vanilla Tahitensis Fruit Extract, Benzyl Alcohol, Sansevieria Trifasciata Leaf Extract, Portulaca Oleracea Extract, Sorbic Acid, Ethylhexylglycerin, Potassium Sorbate, Dehydroacetic Acid, Sodium Benzoate